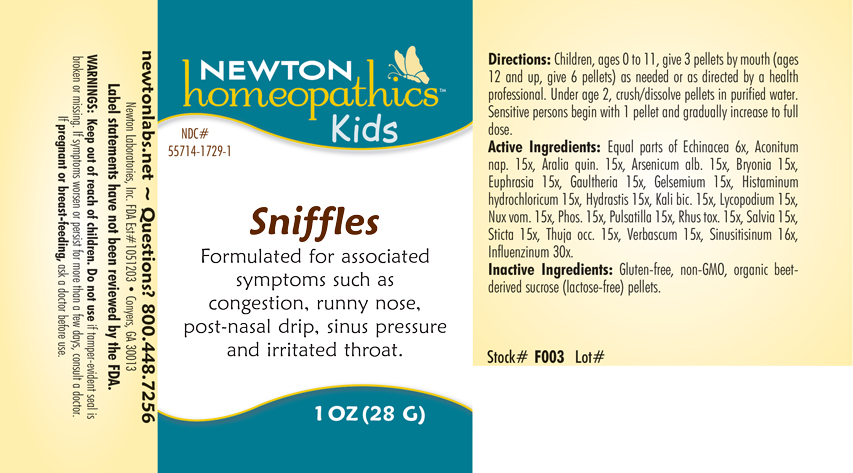 DRUG LABEL: Sniffles
NDC: 55714-1729 | Form: PELLET
Manufacturer: Newton Laboratories, Inc.
Category: homeopathic | Type: HUMAN OTC DRUG LABEL
Date: 20250128

ACTIVE INGREDIENTS: ECHINACEA, UNSPECIFIED 6 [hp_X]/1 g; STRYCHNOS NUX-VOMICA SEED 15 [hp_X]/1 g; AMERICAN GINSENG 15 [hp_X]/1 g; ARSENIC TRIOXIDE 15 [hp_X]/1 g; BRYONIA ALBA ROOT 15 [hp_X]/1 g; EUPHRASIA STRICTA 15 [hp_X]/1 g; GAULTHERIA PROCUMBENS TOP 15 [hp_X]/1 g; GELSEMIUM SEMPERVIRENS ROOT 15 [hp_X]/1 g; HISTAMINE DIHYDROCHLORIDE 15 [hp_X]/1 g; GOLDENSEAL 15 [hp_X]/1 g; POTASSIUM DICHROMATE 15 [hp_X]/1 g; LYCOPODIUM CLAVATUM SPORE 15 [hp_X]/1 g; ANEMONE PULSATILLA 15 [hp_X]/1 g; TOXICODENDRON PUBESCENS LEAF 15 [hp_X]/1 g; SAGE 15 [hp_X]/1 g; LOBARIA PULMONARIA 15 [hp_X]/1 g; THUJA OCCIDENTALIS LEAFY TWIG 15 [hp_X]/1 g; VERBASCUM THAPSUS 15 [hp_X]/1 g; SINUSITISINUM 16 [hp_X]/1 g; INFLUENZA A VIRUS 30 [hp_X]/1 g; INFLUENZA B VIRUS 30 [hp_X]/1 g; PHOSPHORUS 15 [hp_X]/1 g; ACONITUM NAPELLUS 15 [hp_X]/1 g
INACTIVE INGREDIENTS: SUCROSE

Sniffles 1729P

INDICATIONS AND USAGE SECTION

Formulated for associated symptoms such as congestion, runny nose, post-nasal drip, sinus pressure and irritated throat.

DOSAGE & ADMINISTRATION SECTION

Directions: Children, ages 0 to 11, give 3 pellets mouth (ages 12 and up, give 6 pellets) as needed or as directed by a health professional. Under age 2, crush/dissolve pellets in purified water. Sensitive person begin with 1 pellet and gradually increase to full dose.

OTC - ACTIVE INGREDIENT SECTION

Equal parts of Echinacea 6x, Aconitum napellus 15x, Aralia quinquefolia 15x, Arsenicum album 15x, Bryonia 15x, Euphrasia officinalis 15x, Gaultheria procumbens 15x, Gelsemium sempervirens 15x, Histaminum hydrochloricum 15x, Hydrastis canadensis 15x, Kali bichromicum 15x, Lycopodium clavatum 15x, Nux vomica 15x, Phosphorus 15x, Pulsatilla 15x, Rhus toxicodendron 15x, Salvia officinalis 15x, Sticta pulmonaria 15x, Thuja occidentalis 15x, Verbascum thapsus 15x, Sinusitisinum 16x, Influenzinum 30x.

OTC - PURPOSE SECTION

Formulated for associated symptoms such as congestion, runny nose, post-nasal drip, sinus pressure and irritated throat.

INACTIVE INGREDIENT SECTION

Gluten-free, non-GMO, organic beet-derived sucrose (lactose-free) pellets.

QUESTIONS SECTION

newtonlabs.net – Questions? 800.448.7256

Newton Laboratories, Inc. FDA Est # 1051203 - Conyers, GA 30013

WARNINGS SECTION

WARNINGS: Keep out of reach of children. Do not use if tamper-evident seal is broken or missing. If symptoms worsen or persist for more than a few days, consult a doctor. If pregnant or breast-feeding, ask a doctor before use.

OTC - PREGNANCY OR BREAST FEEDING SECTION

If pregnant or breast-feeding, ask a doctor before use.

OTC - KEEP OUT OF REACH OF CHILDREN SECTION

WARNINGS: Keep out of reach of children.